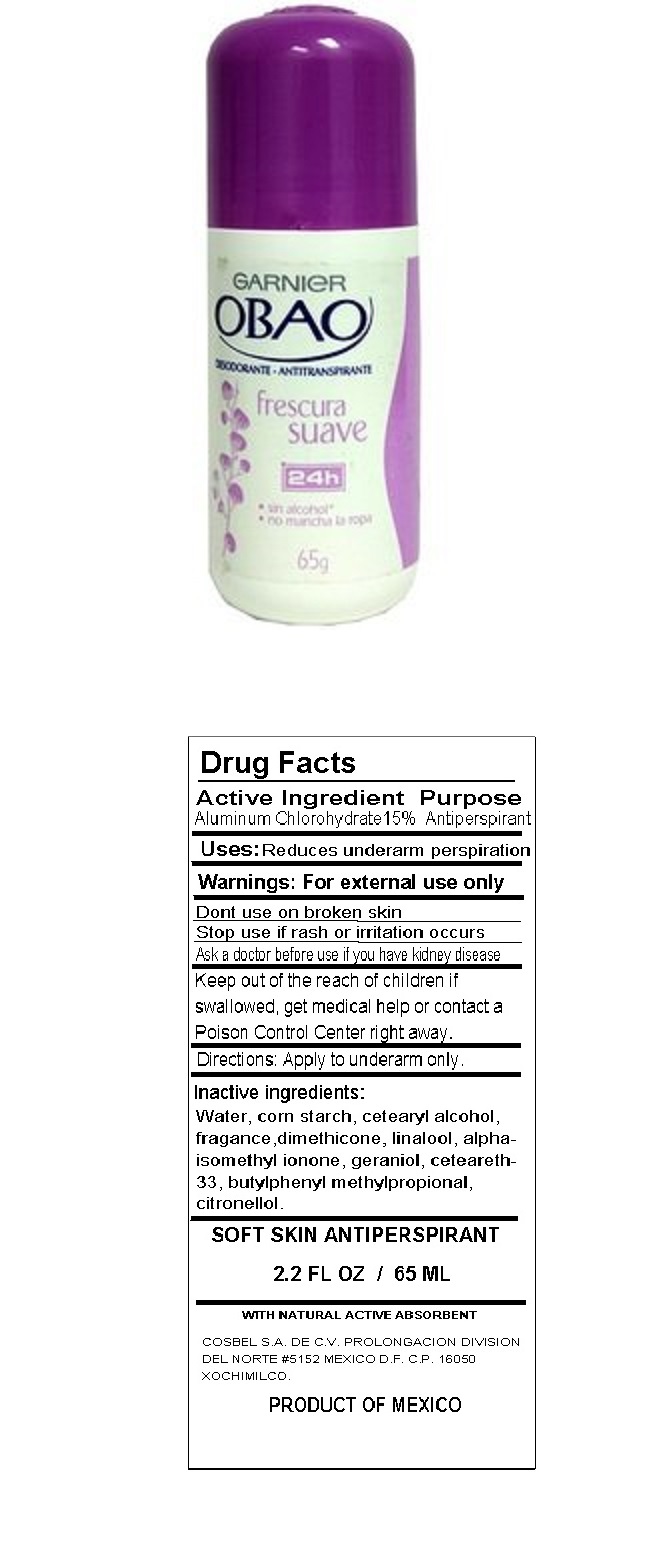 DRUG LABEL: Obao
NDC: 72365-125 | Form: LIQUID
Manufacturer: Promotora De Productos Mexicanos, S.a. De C.v.
Category: otc | Type: HUMAN OTC DRUG LABEL
Date: 20180730

ACTIVE INGREDIENTS: ALUMINUM CHLOROHYDRATE 15 g/100 mL
INACTIVE INGREDIENTS: WATER; STARCH, CORN; CETOSTEARYL ALCOHOL; DIMETHICONE; LINALOOL, (+/-)-; ISOMETHYL-.ALPHA.-IONONE; GERANIOL; CETEARETH-33; BUTYLPHENYL METHYLPROPIONAL; .BETA.-CITRONELLOL, (R)-

OBAO SOFT FRESHNESS

Active Ingredient

Aluminum Chlorohydrate 15%

Purpose

Antiperspirant

Uses:

Reduces underarm perspiration

Warnings:

For external use only

Don't use on broken skin

Stop use if rash or irritation occurs

Ask a doctor before use if you have kidney disease

KEEP OUT OF REACH OF CHILDREN

Keep out of the reach of children if swallowed, get medical help or contact a Poison Control Center right away.

Directions:

Apply to underarm only.

Inactive ingredients:

Water, corn starch, cetearyl alcohol, fragrance, dimethicone, linalool, alpha-isomethyl ionone, geraniol, ceteareth-33, butylphenyl methylpropional, citronellol.

GARNIER

frescura suave

24h

SOFT SKIN ANTIPERSPIRANT

WTH NATURAL ACTIVE ABSORBENT

COSBEL S.A. DE C.V. PROLONGACION DIVISION DEL NORTE #5152 MEXICO D.F. C.P. 16050 XOCHIMILCO.

PRODUCT OF MEXICO